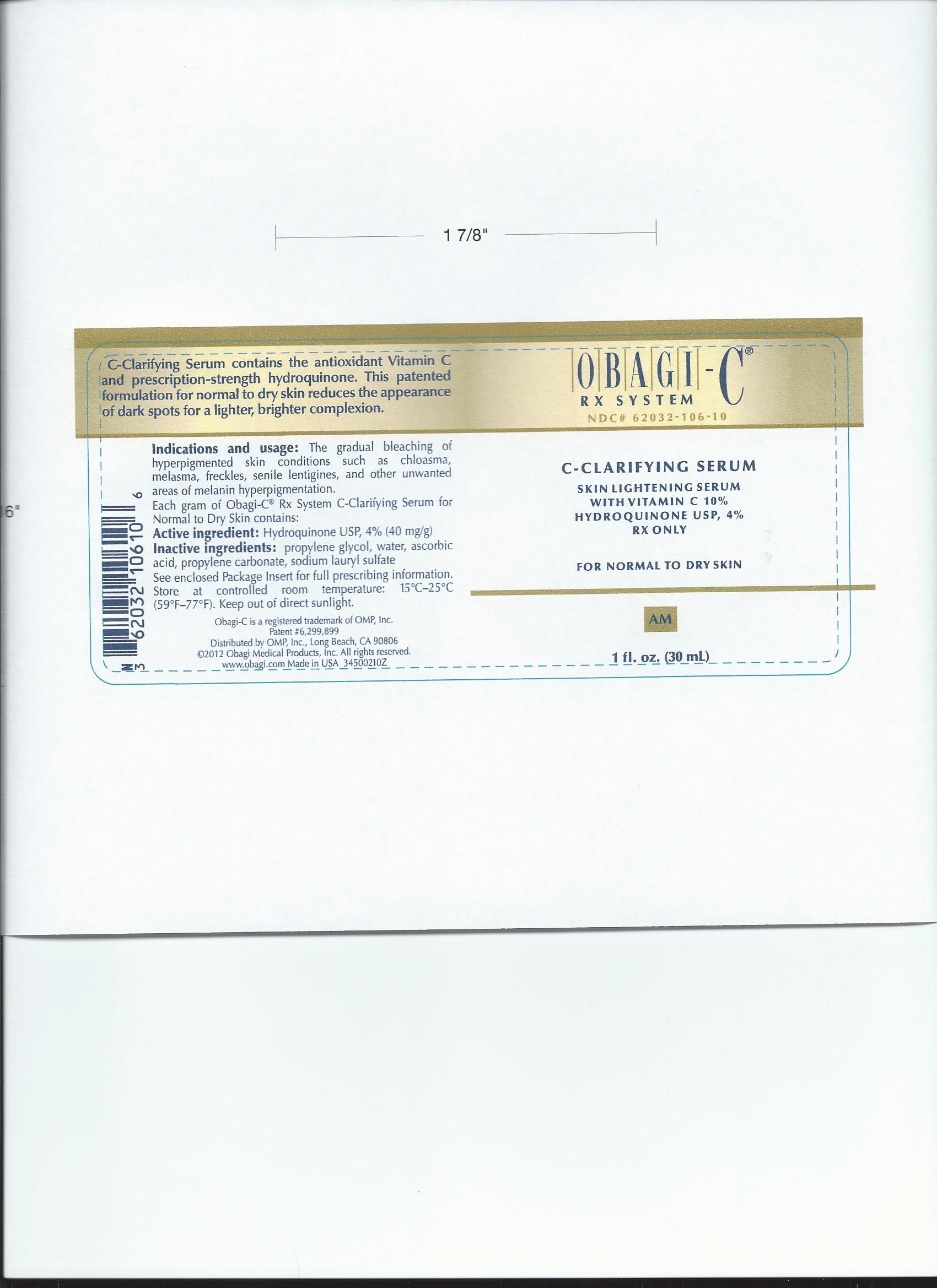 DRUG LABEL: Obagi - C
                
NDC: 69269-106 | Form: LIQUID
Manufacturer: YS PLUS CORPORATION
Category: prescription | Type: HUMAN PRESCRIPTION DRUG LABEL
Date: 20141011

ACTIVE INGREDIENTS: HYDROQUINONE 40 mg/1 mL
INACTIVE INGREDIENTS: PROPYLENE GLYCOL; WATER; ASCORBIC ACID; PROPYLENE CARBONATE; SODIUM LAURYL SULFATE

Drug Facts

WELCOME TO THE OBAGI - C RX SYSTEM OF SKIN CARE PRODUCTS!

For external use only

Rx only

PATIENT INFORMATION

For topical use only

Help correct early signs of aging and skin damage before they become a problem! This early

intervention system helps keep your skin protected and proactively addresses emerging signs of

skin dmaage to refresh and maintain youthful, healthy - looking skin. The Obagi - C Rx System is a

unique skin care regumen that combines the benefits of both prescription - strength

hydroquinone and the power of Vitamin - C.

Please read this product infomration prior to use of the Obagi - C Rx System. Any questions

regarding your particular skin care regimen should be directed to your physician. More

information about the Obagi - C Rx System or other Obagi systems is available at our website at

www.obagi.com.

PATIENT COUNSELING INFORMATION

Each gram of Obagi - C Rx System C - Clarifying Serum for Normal to Dry Skin contains:

Active ingredient:

Hydroquinone USP, 4 % (40 mg / g)

Inactive Ingredients:

propylene glycol, water, ascorbic acid, propylene carbonate, sodium lauryl sulfate

Each gram of Obagi - C Rx System C - Clarifying Serum for Normal to Oily Skin contains:

Active Ingredient:

Hydroquinone USP, 4 % (40 mg / g)

Inactive ingredients:

water, propylene glycol, alcohol denat., dipropylene glycol, ascorbic acid, propylene carbonate,

sodium lauryl sulfate, fragrance

Each gram of Obagi - C Rx System C - Therapy Night Cream contains:

Active ingredient:

Hydroquinone USP, 4 % (40 mg / g)

Inactive Ingredients:

water, glycerin, cetyl alcohol, PPG - 2 myristyl ether propionate, sodium lauryl sulfate, TEA -

salicylate, lactic acid, phenyl trimethicone, tocopheryl acetate, sodium metabisulfite, ascorbic

acid, methylparaben, disodium EDTA, propylparaben, saponins, BHT

DESCRIPTION

Hydroquinone is 1,4 - bensenediol. Hydroquinone occurs as fine, white needles. The drug is freely

soluble in water and in alcohol. Chemically, hydroquinone is designated as p - dihydroxybenzene;

the empirical formula is C6H6O2; molecular weight is 110.11 g / moL.

CLINICAL PHARMACOLOGY

Topical application of hydroquinone produces a reversible depigmentation of the skin by

inhibition of the enzymatic oxidation of 3, 4 - dihydroxyphenylalanine (DOPA) and

suppression of other melanocyte metabolic processes. Exposure to sunlight or ultraviolet light

will cause repigmentation of the bleached areas, which may be prevented by the use of

sunblocking agents or sunscreen agents contained in the Obagi - C Rx System sun Shield Matte

Broad Spectrum SPF 50.

INDICATIONS AND USAGE

The gradual bleaching of hyperpigmented skin conditions such as chloasma, melasma, freckles,

senile lentigines, and other unwanted areas of melanin hyperpigmentation.

DOSAGE AND ADMINISTRATION

A thin application should be applied once or twice daily or as directed by a physician. no

improvement is seen after three (3) months of treatment, use of this product should be

discontinued. Sun exposure may be limited by using a sunscreen agent, a sunblocking agent,

or protective clothing to cover bleached skin when using and after using this product in order to

prevent darkening from reoccuring.

WARNINGS

Hydroquinoone is a skin - bleaching agent, which may produce unwanted cosmetic effects if not

used as directed. The physician should be familiar with the contents of this insert before prescribing

or dispensing this product.

Test for skin sensitivity before using by applying a small amount to an unbroken patch of skin

and check within 24 hours. Minor redness is not a contraindication, but where there is itching

or vesicle formation or excessive inflammatory response, product should be discontinued and

physician consulted. Close patient supervision is recommended.

Avoid contact with eyes, nose, mouth, and lips. In case of accidental contact, patient should

rinse thoroughly with water and contact a physician.

Sunscreen use is an essential aspect of hydroquinone therapy because even minimal sunlight

exposure sustains melanocytic activity.

The Obagi - C Rx Therapy Night Cream contains sodium metabisulfite, a sulfite that

may cause allergic - type reactions including anaphylactic symptoms and life - threatening or

less severe asthmatic episodes in certain susceptible people. The overall prevalence of sulfite

sensitivity in the general populationis unknown and probably low. Sulfite sensitivity is seen

more frequently in asthmatic than in nonasthmatic people.

PRECAUTIONS

(also see WARNINGS)

Treatment should be limited to relatively small areas of the body at one time since some

patients experience a transient skin reddening and a mild burning sensation, which does not

preclude treatment.

Pregnancy Category C

Animal reproduction studies have not been conducted with topical hydroquinone. It is also

not known whether hydroquinone can case fetal harm when used topically on a pregnant woman

or affect reproductive capacity. It is not known to what degree, if any, topical hydroquinone is

absorbed systemically. Topical hydroquinone should be used on pregnant women only when

clearly indicated.

Nursing Mothers

It is not known whether topical hydroquinone is absorbed or excreted in human milk. Caution is

advised when topical hydroquinone is used by a nursing mother.

Pediatric Usage

Safety and effectiveness in children below the age of 12 years have not been established.

ADVERSE REACTIONS

No systemic adverse reactions have been reported. Occasional hypersensitivity (localized

contact dermatitis) may occur, in which case the product should be discontinued and physician

notified immediately.

CONTRAINDICATIONS

People with prior history of sensitivity or allergic reaction to this product or any of its

ingredients should not use it. The safety of topical hydroquinone use during pregnancy

or in children (12 years and under) has not been established.

STORAGE AND HANDLING

Store at controlled room temperature 15 C - 25 C (59 F - 77 F). Keep out of direct sunlight